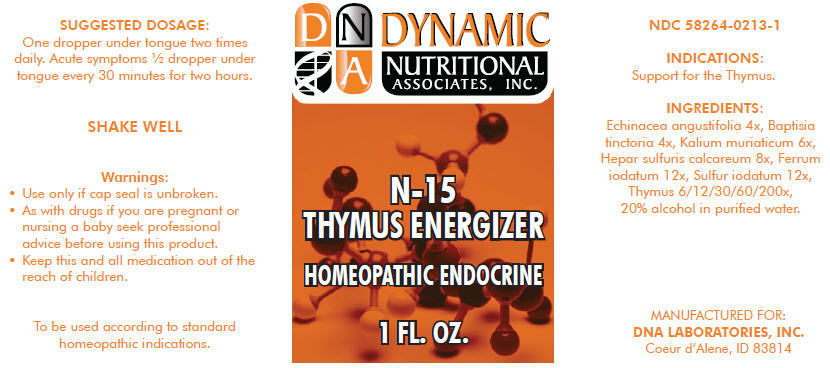 DRUG LABEL: N-15
NDC: 58264-0213 | Form: SOLUTION
Manufacturer: DNA Labs, Inc.
Category: homeopathic | Type: HUMAN OTC DRUG LABEL
Date: 20250109

ACTIVE INGREDIENTS: ECHINACEA ANGUSTIFOLIA 4 [hp_X]/1 mL; BAPTISIA TINCTORIA 4 [hp_X]/1 mL; POTASSIUM CHLORIDE 6 [hp_X]/1 mL; CALCIUM SULFIDE 8 [hp_X]/1 mL; FERROUS IODIDE 12 [hp_X]/1 mL; SULFUR IODIDE 12 [hp_X]/1 mL; BOS TAURUS THYMUS 200 [hp_X]/1 mL
INACTIVE INGREDIENTS: ALCOHOL; WATER

N-15

NDC 58264-0213-1

INDICATIONS

PURPOSE

Support for the Thymus.

ACTIVE INGREDIENT

INGREDIENTS

Echinacea angustifolia 4x, Baptisia tinctoria 4x, Kalium muriaticum 6x, Hepar sulfuris calcareum 8x, Ferrum iodatum 12x, Sulfur iodatum 12x, Thymus 6/12/30/60/200x, 20% alcohol in purified water.

SUGGESTED DOSAGE

One dropper under tongue two times daily. Acute symptoms ½ dropper under tongue every 30 minutes for two hours.

STORAGE AND HANDLING

SHAKE WELL

Warnings

- Use only if cap seal is unbroken.

PREGNANCY OR BREAST FEEDING

- As with drugs if you are pregnant or nursing a baby seek professional advice before using this product.

KEEP OUT OF REACH OF CHILDREN

- Keep this and all medication out of the reach of children.

To be used according to standard homeopathic indications.

PRINCIPAL DISPLAY PANEL - 1 FL. OZ. Bottle Label

DYNAMIC
NUTRITIONAL
ASSOCIATES, INC.

N-15

THYMUS ENERGIZER

HOMEOPATHIC ENDOCRINE

1 FL. OZ.